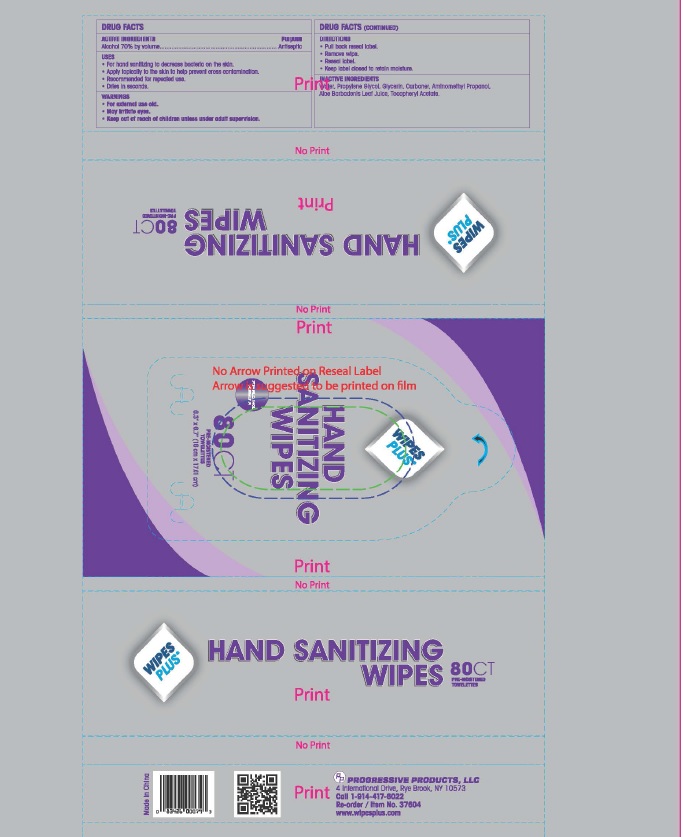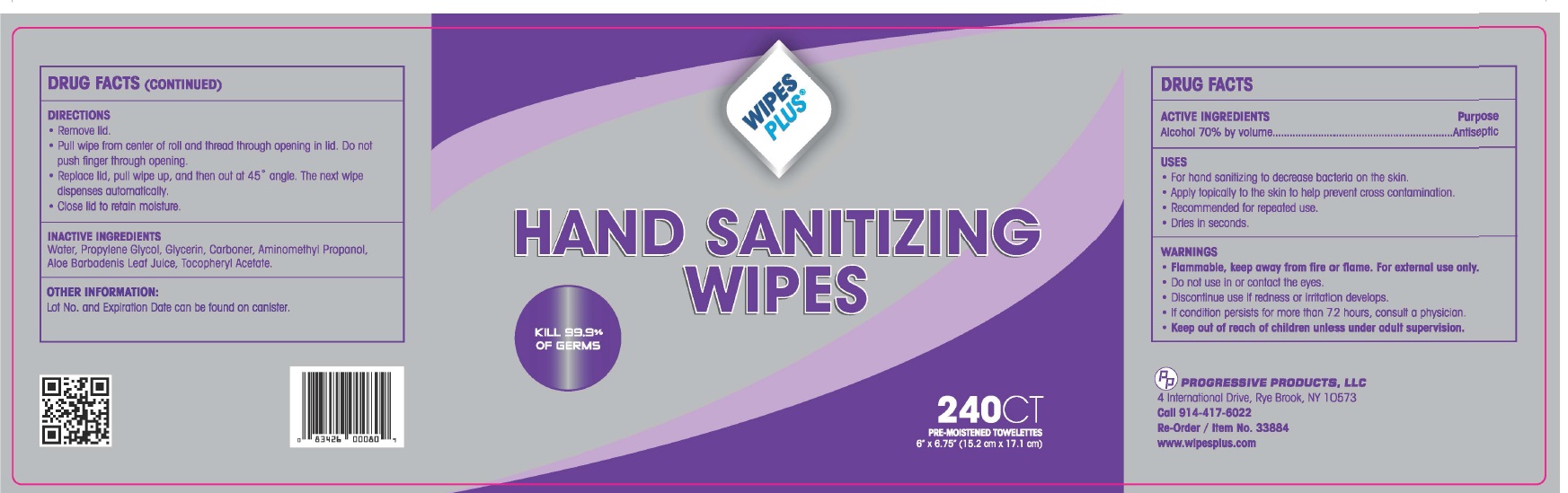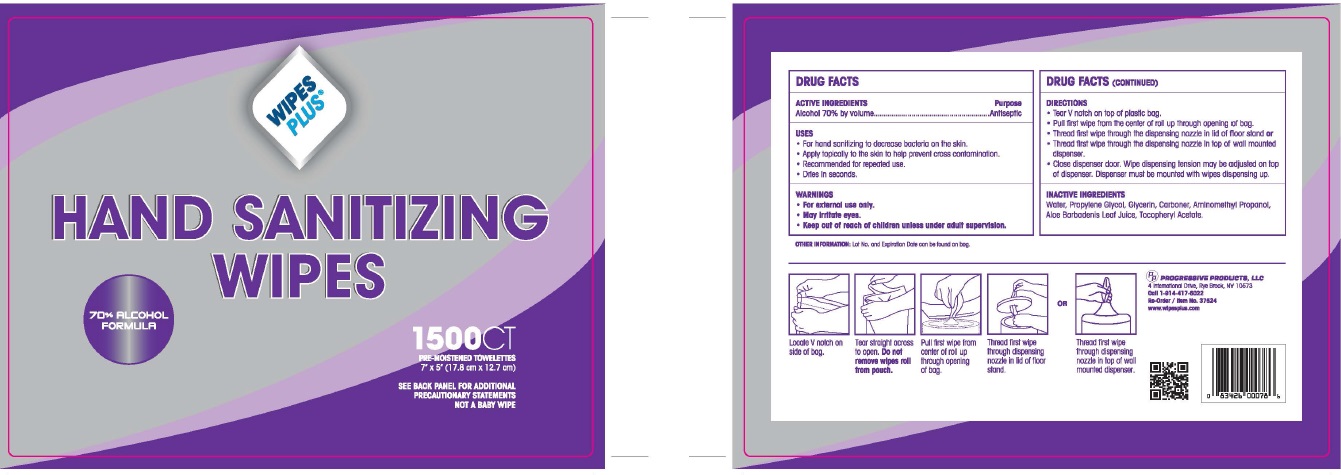 DRUG LABEL: Wipes Plus
NDC: 67151-606 | Form: SWAB
Manufacturer: Progressive Products, LLC
Category: otc | Type: HUMAN OTC DRUG LABEL
Date: 20221014

ACTIVE INGREDIENTS: ALCOHOL 70 mL/100 mL
INACTIVE INGREDIENTS: WATER; PROPYLENE GLYCOL; AMINOMETHYLPROPANOL; ALOE VERA LEAF; .ALPHA.-TOCOPHEROL ACETATE

DRUG FACTS

Active Ingredient

Alcohol 70% by volume

Purpose

Antiseptic

Uses

• For hand sanitizing to decrease bacteria on the skin.
• Apply topically to the skin to help prevent cross contamination.
• Recommended for repeated use.
• Dries In seconds.

Warnings

- Flammable, keep away from fire or flame. For external use only.
- Do not use In or contact the eyes.
- Discontinue use If redness or Irritation develops.
- If condition persists for more than 72 hours, consult a physician.

Keep our of reach of children

Keep out of reach of chlldren unless under adult supervision.

Directions

•Remove lld.
• Pull wipe from center of roll and thread through opening in lid. Do not
push finger through opening.
• Replace lld, pull wipe up, and then out at 45 • angle. The next wipe
dispenses automatically.
• Close lld to retain moisture.

Inactive Ingredients

Water, Propylene Glycol, Glycerin, Carboner, Aminomethyl Propanol, Aloe Barbadenis Leaf Juice, Tocopheryl Acetate.

Questions or Comments

Lot No. and Expiration Date can be found on canister.

@PROGRESSIVE PRODUCTS, LLC
4 International Drive, Rye Brook, NY 1 0573
CGll 914-417-6022
Re-order/Item No. 33884
www.wlpesplus.com

Principal Display Panel

NDC 67151-606-01

RE-ORDER/ITEM NO 37604

NDC 67151-606-02

RE-ORDER/ITEM NO 33884

NDC 67151-606-03

RE-ORDER/ITEM NO 37524